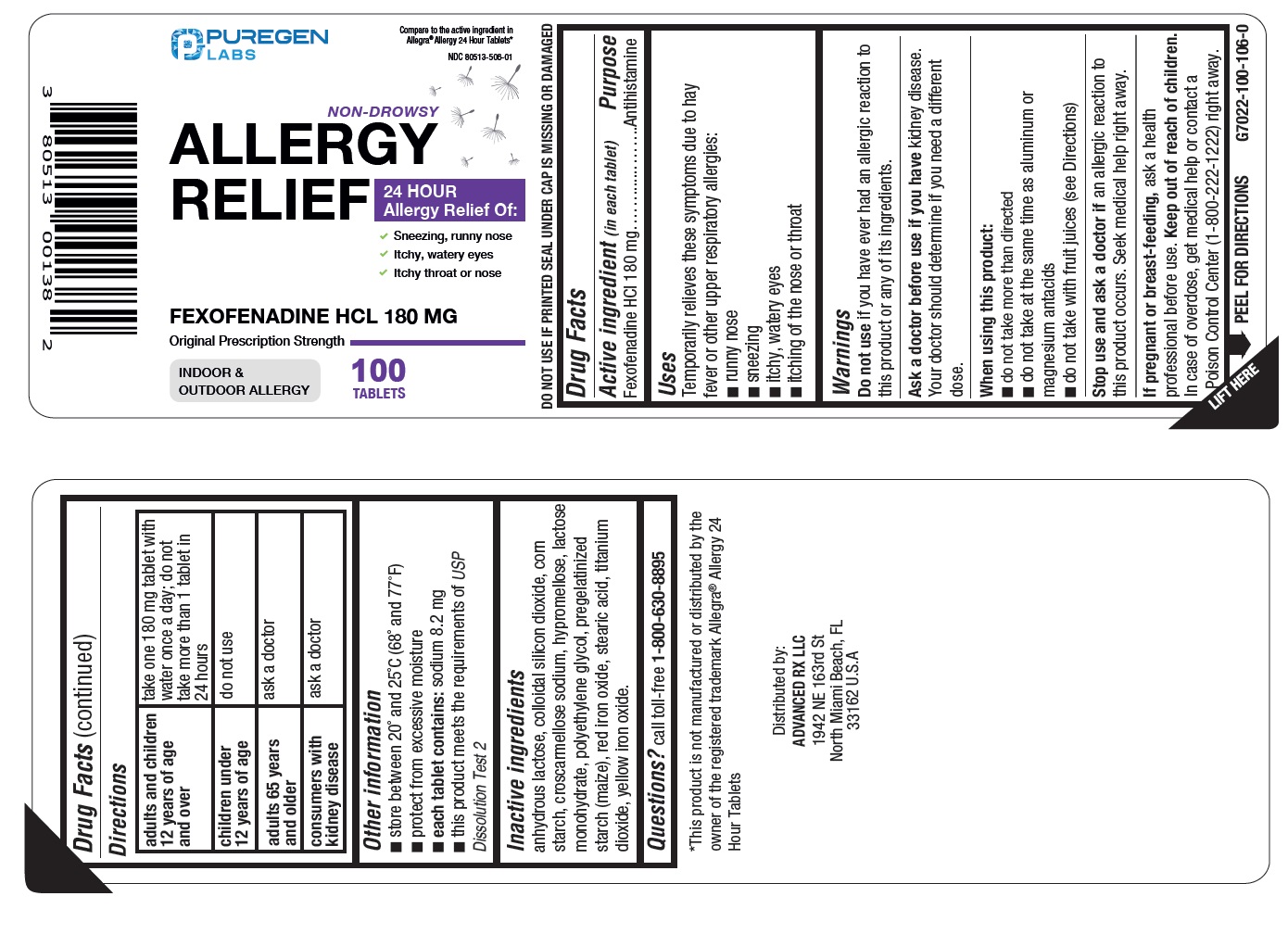 DRUG LABEL: Fexofenadine HCl
NDC: 80513-506 | Form: TABLET, FILM COATED
Manufacturer: Advanced Rx LLC
Category: otc | Type: HUMAN OTC DRUG LABEL
Date: 20240910

ACTIVE INGREDIENTS: FEXOFENADINE HYDROCHLORIDE 180 mg/1 1
INACTIVE INGREDIENTS: ANHYDROUS LACTOSE; SILICON DIOXIDE; STARCH, CORN; CROSCARMELLOSE SODIUM; LACTOSE MONOHYDRATE; STEARIC ACID; HYPROMELLOSE, UNSPECIFIED; POLYETHYLENE GLYCOL, UNSPECIFIED; FERRIC OXIDE RED; TITANIUM DIOXIDE; FERRIC OXIDE YELLOW

Active ingredient (in each tablet)

Fexofenadine HCl 180 mg

Purpose

Antihistamine

Uses

Temporarily relieves these symptoms due to hay fever or other upper respiratory allergies:

- runny nose
- sneezing
- itchy, watery eyes
- itching of the nose or throat

Warnings

Do not use

if you have ever had an allergic reaction to this product or any of its ingredients.

Ask a doctor before use if you have

kidney disease. Your doctor should determine if you need a different dose.

When using this product

- do not take more than directed
- do not take at the same time as aluminum or magnesium antacids
- do not take with fruit juices (see Directions)

Stop use and ask a doctor if

an allergic reaction to this product occurs. Seek medical help right away.

PREGNANCY OR BREAST FEEDING

If pregnant or breast-feeding,ask a health professional before use.

Keep out of reach of children.

In case of overdose, get medical help or contact a Poison Control Center (1-800-222-1222) right away.

Directions

adults and children 12 years of age and over | take one 180mg tablet with water once a day; do not take more than 1 tablet in 24 hours
children under 12 years of age | do not use
adults 65 years of age and older | ask a doctor
consumers with kidney disease | ask a doctor

Other information

- store between 20° and 25°C (68° and 77°F)
- protect from excessive moisture
- each tablet contains:sodium 8.2 mg
- this product meets the requirements of USPDissolution Test 2
- DO NOT USE IF PRINTED SEAL UNDER CAP IS MISSING OR DAMAGED

Inactive ingredients

anhydrous lactose, colloidal silicon dioxide, corn starch, croscarmellose sodium, hypromellose, lactose monohydrate, polyethylene glycol, pregelatinized starch (maize), red iron oxide, stearic acid, titanium dioxide, and yellow iron oxide

Questions?

call toll free 1-800-630-8895

Distributed by:

Advanced Rx LLC

1942 NE 163rd St North Miami Beach,

FL 33162 U.S.A.

Package/Label Principal Display Panel

NDC 80513-506-01

Compare to the active ingredient in Allegra®Allergy 24 Hour Tablets*

Non-Drowsy

Allergy Relief

Fexofenadine HCL 180 mg

INDOOR & OUTDOOR ALLERGY

24-Hour Allergy Relief Of:

- Sneezing, runny nose
- Itchy, watery eyes
- Itchy throat or nose

100 Tablets

*This product is not manufactured or distributed by the owner of the registered trademark Allegra®Allergy 24 Hour Tablets.